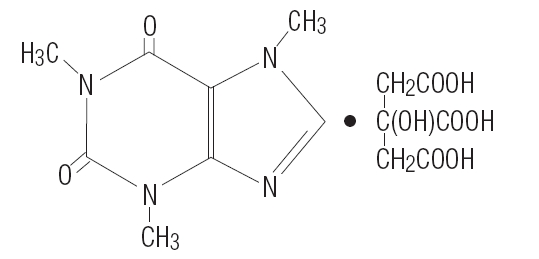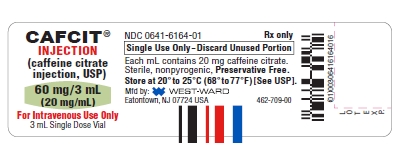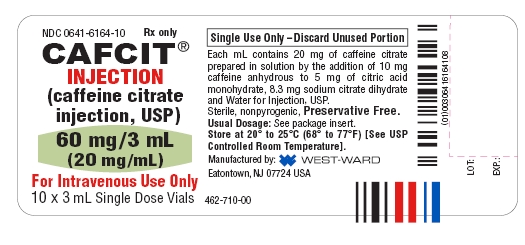 DRUG LABEL: CAFCIT
NDC: 0641-6164 | Form: INJECTION
Manufacturer: Hikma Pharmaceuticals USA Inc.
Category: prescription | Type: HUMAN PRESCRIPTION DRUG LABEL
Date: 20260302

ACTIVE INGREDIENTS: CAFFEINE CITRATE 20 mg/1 mL
INACTIVE INGREDIENTS: CITRIC ACID MONOHYDRATE 5 mg/1 mL; SODIUM CITRATE 8.3 mg/1 mL; WATER

Caffeine Citrate Injection, USP

Rx only

DESCRIPTION

CAFCIT® Injection (caffeine citrate injection, USP) for intravenous administration is a clear, colorless, sterile, non-pyrogenic, preservative-free, aqueous solution adjusted to pH 4.7. Each mL contains 20 mg caffeine citrate (equivalent to 10 mg of caffeine base) prepared in solution by the addition of 10 mg caffeine anhydrous to 5 mg citric acid monohydrate, 8.3 mg sodium citrate dihydrate and Water for Injection, USP.

Caffeine, a central nervous system stimulant, is an odorless white crystalline powder or granule, with a bitter taste. It is sparingly soluble in water and ethanol at room temperature. The chemical name of caffeine is 3,7-dihydro-1,3,7-trimethyl-1H-purine-2,6-dione. In the presence of citric acid it forms caffeine citrate salt in solution. The structural formula and molecular weight of caffeine citrate follows.

Caffeine citrate

C14H18N4O9 MW 386.31

CLINICAL PHARMACOLOGY

Mechanism of Action

Caffeine is structurally related to other methylxanthines, theophylline, and theobromine. It is a bronchial smooth muscle relaxant, a CNS stimulant, a cardiac muscle stimulant, and a diuretic.

Although the mechanism of action of caffeine in apnea of prematurity is not known, several mechanisms have been hypothesized. These include: (1) stimulation of the respiratory center, (2) increased minute ventilation, (3) decreased threshold to hypercapnia, (4) increased response to hypercapnia, (5) increased skeletal muscle tone, (6) decreased diaphragmatic fatigue, (7) increased metabolic rate, and (8) increased oxygen consumption.

Most of these effects have been attributed to antagonism of adenosine receptors, both A1 and A2 subtypes, by caffeine, which has been demonstrated in receptor binding assays and observed at concentrations approximating those achieved therapeutically.

Pharmacokinetics

Absorption

After oral administration of 10 mg caffeine base/kg to preterm neonates, the peak plasma level (Cmax) for caffeine ranged from 6 to 10 mg/L and the mean time to reach peak concentration (Tmax) ranged from 30 minutes to 2 hours. The Tmax was not affected by formula feeding. The absolute bioavailability, however, was not fully examined in preterm neonates.

Distribution

Caffeine is rapidly distributed into the brain. Caffeine levels in the cerebrospinal fluid of preterm neonates approximate their plasma levels. The mean volume of distribution of caffeine in infants (0.8 to 0.9 L/kg) is slightly higher than that in adults (0.6 L/kg). Plasma protein binding data are not available for neonates or infants. In adults, the mean plasma protein binding in vitro is reported to be approximately 36%.

Metabolism

Hepatic cytochrome P450 1A2 (CYP1A2) is involved in caffeine biotransformation. Caffeine metabolism in preterm neonates is limited due to their immature hepatic enzyme systems.

Interconversion between caffeine and theophylline has been reported in preterm neonates; caffeine levels are approximately 25% of theophylline levels after theophylline administration and approximately 3 to 8% of caffeine administered would be expected to convert to theophylline.

Elimination

In young infants, the elimination of caffeine is much slower than that in adults due to immature hepatic and/or renal function. Mean half-life (T1/2) and fraction excreted unchanged in urine (Ae) of caffeine in infants have been shown to be inversely related to gestational/postconceptual age. In neonates, the T1/2 is approximately 3 to 4 days and the Ae is approximately 86% (within 6 days). By 9 months of age, the metabolism of caffeine approximates that seen in adults (T1/2 = 5 hours and Ae = 1%).

Special Populations

Studies examining the pharmacokinetics of caffeine in neonates with hepatic or renal insufficiency have not been conducted. CAFCIT (caffeine citrate) should be administered with caution in preterm neonates with impaired renal or hepatic function. Serum concentrations of caffeine should be monitored and dose administration of CAFCIT should be adjusted to avoid toxicity in this population.

Clinical Studies

One multicenter, randomized, double-blind trial compared CAFCIT (caffeine citrate) to placebo in eighty-five (85) preterm infants (gestational age 28 to <33 weeks) with apnea of prematurity. Apnea of prematurity was defined as having at least 6 apnea episodes of greater than 20 seconds duration in a 24-hour period with no other identifiable cause of apnea. A 1 mL/kg (20 mg/kg caffeine citrate providing 10 mg/kg as caffeine base) loading dose of CAFCIT was administered intravenously, followed by a 0.25 mL/kg (5 mg/kg caffeine citrate providing 2.5 mg/kg of caffeine base) daily maintenance dose administered either intravenously or orally (generally through a feeding tube). The duration of treatment in this study was limited to 10 to 12 days. The protocol allowed infants to be "rescued" with open-label caffeine citrate treatment if their apnea remained uncontrolled during the double-blind phase of the trial.

The percentage of patients without apnea on day 2 of treatment (24 to 48 hours after the loading dose) was significantly greater with CAFCIT than placebo. The following table summarizes the clinically relevant endpoints evaluated in this study:

 | CAFCIT | Placebo | p-value
Number of patients evaluated^1 | 45 | 37 | -
% of patients with zero apnea events on day 2 | 26.7 | 8.1 | 0.03
Apnea rate on day 2 (per 24 h) | 4.9 | 7.2 | 0.134
% of patients with 50% reduction in apnea events from baseline on day 2 | 76 | 57 | 0.07

^1 Of 85 patients who received drug, 3 were not included in the efficacy analysis because they had <6 apnea episodes/24 hours at baseline.

In this 10 to 12 day trial, the mean number of days with zero apnea events was 3 in the CAFCIT group and 1.2 in the placebo group. The mean number of days with a 50% reduction from baseline in apnea events was 6.8 in the CAFCIT group and 4.6 in the placebo group.

INDICATIONS AND USAGE

CAFCIT (caffeine citrate) is indicated for the treatment of apnea of prematurity.

CONTRAINDICATIONS

CAFCIT (caffeine citrate) is contraindicated in patients who have demonstrated hypersensitivity to any of its components.

WARNINGS

Necrotizing Enterocolitis

During the double-blind, placebo-controlled clinical trial, 6 cases of necrotizing enterocolitis developed among the 85 infants studied (caffeine=46, placebo=39), with 3 cases resulting in death. Five of the six patients with necrotizing enterocolitis were randomized to or had been exposed to CAFCIT (caffeine citrate).

Reports in the published literature have raised a question regarding the possible association between the use of methylxanthines and development of necrotizing enterocolitis, although a causal relationship between methylxanthine use and necrotizing enterocolitis has not been established. In a published randomized, placebo-controlled, clinical trial that studied the use of caffeine citrate in apnea of prematurity in approximately 2000 patients, necrotizing enterocolitis was not more common in caffeine treated patients compared to placebo. As with all preterm infants, patients being treated with CAFCIT should be carefully monitored for the development of necrotizing enterocolitis.

PRECAUTIONS

General

Apnea of prematurity is a diagnosis of exclusion. Other causes of apnea (e.g., central nervous system disorders, primary lung disease, anemia, sepsis, metabolic disturbances, cardiovascular abnormalities, or obstructive apnea) should be ruled out or properly treated prior to initiation of CAFCIT (caffeine citrate).

Caffeine is a central nervous system stimulant and in cases of caffeine overdose, seizures have been reported. CAFCIT should be used with caution in infants with seizure disorders.

The duration of treatment of apnea of prematurity in the placebo-controlled trial was limited to 10 to 12 days. The efficacy of CAFCIT for longer periods of treatment has not been established. Safety and efficacy of CAFCIT for use in the prophylactic treatment of sudden infant death syndrome (SIDS) or prior to extubation in mechanically ventilated infants have also not been established.

Cardiovascular

Although no cases of cardiac toxicity were reported in the placebo-controlled trial, caffeine has been shown to increase heart rate, left ventricular output, and stroke volume in published studies. Therefore, CAFCIT should be used with caution in infants with cardiovascular disease.

Renal and Hepatic Systems

CAFCIT should be administered with caution in infants with impaired renal or hepatic function. Serum concentrations of caffeine should be monitored and dose administration of CAFCIT should be adjusted to avoid toxicity in this population. (See CLINICAL PHARMACOLOGY, Elimination and Special Populations.)

Laboratory Tests

Prior to initiation of CAFCIT (caffeine citrate), baseline serum levels of caffeine should be measured in infants previously treated with theophylline, since preterm infants metabolize theophylline to caffeine. Likewise, baseline serum levels of caffeine should be measured in infants born to mothers who consumed caffeine prior to delivery, since caffeine readily crosses the placenta.

In the placebo-controlled clinical trial, caffeine levels ranged from 8 to 40 mg/L. A therapeutic plasma concentration range of caffeine could not be determined from the placebo-controlled clinical trial. Serious toxicity has been reported in the literature when serum caffeine levels exceed 50 mg/L. Serum concentrations of caffeine may need to be monitored periodically throughout treatment to avoid toxicity.

In clinical studies reported in the literature, cases of hypoglycemia and hyperglycemia have been observed. Therefore, serum glucose may need to be periodically monitored in infants receiving CAFCIT.

Drug Interactions

Cytochrome P450 1A2 (CYP1A2) is known to be the major enzyme involved in the metabolism of caffeine. Therefore, caffeine has the potential to interact with drugs that are substrates for CYP1A2, inhibit CYP1A2, or induce CYP1A2.

Few data exist on drug interactions with caffeine in preterm neonates. Based on adult data, lower doses of caffeine may be needed following coadministration of drugs which are reported to decrease caffeine elimination (e.g., cimetidine and ketoconazole) and higher caffeine doses may be needed following coadministration of drugs that increase caffeine elimination (e.g., phenobarbital and phenytoin).

Caffeine administered concurrently with ketoprofen reduced the urine volume in four healthy volunteers. The clinical significance of this interaction in preterm neonates is not known.

Interconversion between caffeine and theophylline has been reported in preterm neonates. The concurrent use of these drugs is not recommended.

Carcinogenesis, Mutagenesis, Impairment of Fertility

In a 2-year study in Sprague-Dawley rats, caffeine (as caffeine base) administered in drinking water was not carcinogenic in male rats at doses up to 102 mg/kg or in female rats at doses up to 170 mg/kg (approximately 2 and 4 times, respectively, the maximum recommended intravenous loading dose for infants on a mg/m^2 basis). In an 18-month study in C57BL/6 mice, no evidence of tumorigenicity was seen at dietary doses up to 55 mg/kg (less than the maximum recommended intravenous loading dose for infants on a mg/m^2 basis).

Caffeine (as caffeine base) increased the sister chromatid exchange (SCE) SCE/cell metaphase (exposure time dependent) in an in vivo mouse metaphase analysis. Caffeine also potentiated the genotoxicity of known mutagens and enhanced the micronuclei formation (5-fold) in folate-deficient mice. However, caffeine did not increase chromosomal aberrations in in vitro Chinese hamster ovary cell (CHO) and human lymphocyte assays and was not mutagenic in an in vitro CHO/hypoxanthine guanine phosphoribosyltransferase (HGPRT) gene mutation assay, except at cytotoxic concentrations. In addition, caffeine was not clastogenic in an in vivo mouse micronucleus assay.

Caffeine (as caffeine base) administered to male rats at 50 mg/kg/day subcutaneously (approximately equal to the maximum recommended intravenous loading dose for infants on a mg/m^2 basis) for 4 days prior to mating with untreated females, caused decreased male reproductive performance in addition to causing embryotoxicity. In addition, long-term exposure to high oral doses of caffeine (3 g over 7 weeks) was toxic to rat testes as manifested by spermatogenic cell degeneration.

Pregnancy

Pregnancy Category C

Concern for the teratogenicity of caffeine is not relevant when administered to infants. In studies performed in adult animals, caffeine (as caffeine base) administered to pregnant mice as sustained release pellets at 50 mg/kg (less than the maximum recommended intravenous loading dose for infants on a mg/m^2 basis), during the period of organogenesis, caused a low incidence of cleft palate and exencephaly in the fetuses. There are no adequate and well-controlled studies in pregnant women.

ADVERSE REACTIONS

Overall, the reported number of adverse events in the double-blind period of the controlled trial was similar for the CAFCIT (caffeine citrate) and placebo groups. The following table shows adverse events that occurred in the double-blind period of the controlled trial and that were more frequent in CAFCIT-treated patients than placebo.

ADVERSE EVENTS THAT OCCURRED MORE FREQUENTLY IN CAFCIT-TREATED PATIENTS THAN PLACEBO DURING DOUBLE-BLIND THERAPY
Adverse Event (AE) | CAFCIT N=46; n (%) | Placebo N=39; n (%)
BODY AS A WHOLE
Accidental Injury | 1 (2.2) | 0 (0.0)
Feeding Intolerance | 4 (8.7) | 2 (5.1)
Sepsis | 2 (4.3) | 0 (0.0)
CARDIOVASCULAR SYSTEM
Hemorrhage | 1 (2.2) | 0 (0.0)
DIGESTIVE SYSTEM
Necrotizing Enterocolitis | 2 (4.3) | 1 (2.6)
Gastritis | 1 (2.2) | 0 (0.0)
Gastrointestinal Hemorrhage | 1 (2.2) | 0 (0.0)
HEMIC AND LYMPHATIC SYSTEM
Disseminated Intravascular Coagulation | 1 (2.2) | 0 (0.0)
METABOLIC AND NUTRITIVE DISORDERS
Acidosis | 1 (2.2) | 0 (0.0)
Healing Abnormal | 1 (2.2) | 0 (0.0)
NERVOUS SYSTEM
Cerebral Hemorrhage | 1 (2.2) | 0 (0.0)
RESPIRATORY SYSTEM
Dyspnea | 1 (2.2) | 0 (0.0)
Lung Edema | 1 (2.2) | 0 (0.0)
SKIN AND APPENDAGES
Dry Skin | 1 (2.2) | 0 (0.0)
Rash | 4 (8.7) | 3 (7.7)
Skin Breakdown | 1 (2.2) | 0 (0.0)
SPECIAL SENSES
Retinopathy of Prematurity | 1 (2.2) | 0 (0.0)
UROGENITAL SYSTEM
Kidney Failure | 1 (2.2) | 0 (0.0)

In addition to the cases above, three cases of necrotizing enterocolitis were diagnosed in patients receiving CAFCIT (caffeine citrate) during the open-label phase of the study.

Three of the infants who developed necrotizing enterocolitis during the trial died. All had been exposed to caffeine. Two were randomized to caffeine, and one placebo patient was “rescued” with open-label caffeine for uncontrolled apnea.

Adverse events described in the published literature include: central nervous system stimulation (i.e., irritability, restlessness, jitteriness), cardiovascular effects (i.e., tachycardia, increased left ventricular output, and increased stroke volume), gastrointestinal effects (i.e., increased gastric aspirate, gastrointestinal intolerance), alterations in serum glucose (i.e., hypoglycemia and hyperglycemia), and renal effects (i.e., increased urine flow rate, increased creatinine clearance, and increased sodium and calcium excretion). Published long-term follow-up studies have not shown caffeine to adversely affect neurological development or growth parameters.

A published randomized, placebo-controlled, clinical trial in premature infants with birthweights of 500-1250 grams studied the safety of caffeine citrate in apnea of prematurity (NCT00182312). This trial randomized approximately 2000 premature infants with a mean gestational age of 27 weeks at birth. The median duration of caffeine therapy was 37 days. Prior to discharge home, death, ultrasonographic signs of brain injury, and necrotizing enterocolitis were not more common in the caffeine citrate group compared to the placebo. At follow up at both 18 months and 5 years corrected age, death was not more common in the caffeine citrate treated group compared to placebo, nor did caffeine citrate use adversely affect neurodevelopmental outcomes.

OVERDOSAGE

Following overdose, serum caffeine levels have ranged from approximately 24 mg/L (a postmarketing spontaneous case report in which an infant exhibited irritability, poor feeding, and insomnia) to 350 mg/L. Serious toxicity has been associated with serum levels greater than 50 mg/L (see PRECAUTIONS, Laboratory Tests and DOSAGE AND ADMINISTRATION). Signs and symptoms reported in the literature after caffeine overdose in preterm infants include fever, tachypnea, jitteriness, insomnia, fine tremor of the extremities, hypertonia, opisthotonos, tonic-clonic movements, nonpurposeful jaw and lip movements, vomiting, hyperglycemia, elevated blood urea nitrogen, and elevated total leukocyte concentration. Seizures have also been reported in cases of overdose. One case of caffeine overdose complicated by development of intraventricular hemorrhage and long-term neurological sequelae has been reported. Another case of caffeine citrate overdose (from New Zealand; not CAFCIT) of an estimated 600 mg caffeine citrate (approximately 322 mg/kg) administered over 40 minutes was complicated by tachycardia, ST depression, respiratory distress, heart failure, gastric distention, acidosis, and a severe extravasation burn with tissue necrosis at the peripheral intravenous injection site. No deaths associated with caffeine overdose have been reported in preterm infants.

Treatment of caffeine overdose is primarily symptomatic and supportive. Caffeine levels have been shown to decrease after exchange transfusions. Convulsions may be treated with intravenous administration of diazepam or a barbiturate such as pentobarbital sodium.

DOSAGE AND ADMINISTRATION

Prior to initiation of CAFCIT (caffeine citrate), baseline serum levels of caffeine should be measured in infants previously treated with theophylline, since preterm infants metabolize theophylline to caffeine. Likewise, baseline serum levels of caffeine should be measured in infants born to mothers who consumed caffeine prior to delivery, since caffeine readily crosses the placenta.

The recommended loading dose and maintenance doses of CAFCIT follow.

 | Dose of CAFCIT (caffeine citrate) Volume | Dose of CAFCIT (caffeine citrate) mg/kg | Route | Frequency
Loading Dose | 1 mL/kg | 20 mg/kg | Intravenous* (over 30 minutes) | One time
Maintenance Dose | 0.25 mL/kg | 5 mg/kg | Intravenous* (over 10 minutes) or Orally | Every 24 hours**

*Using a syringe infusion pump
**Beginning 24 hours after the loading dose

NOTE THAT THE DOSE OF CAFFEINE BASE IS ONE-HALF THE DOSE WHEN EXPRESSED AS CAFFEINE CITRATE (e.g., 20 mg of caffeine citrate is equivalent to 10 mg of caffeine base).

Serum concentrations of caffeine may need to be monitored periodically throughout treatment to avoid toxicity. Serious toxicity has been associated with serum levels greater than 50 mg/L.

CAFCIT should be inspected visually for particulate matter and discoloration prior to administration. Vials containing discolored solution or visible particulate matter should be discarded.

Drug Compatibility

To test for drug compatibility with common intravenous solutions or medications, 20 mL of CAFCIT Injection were combined with 20 mL of a solution or medication, with the exception of an Intralipid® admixture, which was combined as 80 mL/80 mL. The physical appearance of the combined solutions was evaluated for precipitation. The admixtures were mixed for 10 minutes and then assayed for caffeine. The admixtures were then continually mixed for 24 hours, with further sampling for caffeine assays at 2, 4, 8, and 24 hours.

Based on this testing, CAFCIT Injection, 60 mg/3 mL is chemically stable for 24 hours at room temperature when combined with the following test products.

• Dextrose Injection, USP 5%

• 50% Dextrose Injection USP

• Intralipid® 20% IV Fat Emulsion

• Aminosyn® 8.5% Crystalline Amino Acid Solution

• Dopamine HCI Injection, USP 40 mg/mL diluted to 0.6 mg/mL with Dextrose Injection, USP 5%

• Calcium Gluconate Injection, USP 10% (0.465 mEq/Ca^+2/mL)

• Heparin Sodium Injection, USP 1000 units/mL diluted to 1 unit/mL with Dextrose Injection, USP 5%

• Fentanyl Citrate Injection, USP 50 mcg/mL diluted to 10 mcg/mL with Dextrose Injection, USP 5%

HOW SUPPLIED

CAFCIT® Injection (caffeine citrate injection, USP) is available as a clear, colorless, sterile, non-pyrogenic, preservative-free, aqueous solution in 3 mL colorless glass vials. The vials are sealed with a teflon-faced gray rubber stopper and an aluminum overseal with a white flip-off printed with “FOR INTRAVENOUS USE ONLY” in red.

The vials contain 3 mL solution at a concentration of 20 mg/mL caffeine citrate (60 mg/vial) equivalent to 10 mg/mL caffeine base (30 mg/vial).

CAFCIT® Injection (caffeine citrate injection, USP) is supplied as:

NDC 0641-6164-10, 3 mL Single Dose Vial packaged in a carton of 10

Store at 20° to 25°C (68° to 77°F) [See USP Controlled Room Temperature].

Not made with natural rubber latex.

Preservative free. For single dose only. Discard unused portion.

To report SUSPECTED ADVERSE REACTIONS, contact Hikma Pharmaceuticals USA Inc. at 1-877-845-0689, or the FDA at 1-800-FDA-1088 or www.fda.gov/medwatch.

For Product Inquiry call 1-877-845-0689.

Manufactured by:

Hikma Pharmaceuticals USA Inc.

Eatontown, NJ 07724 USA

Revised December 2019

462-708-01

PRINCIPAL DISPLAY PANELS

CAFCIT®
INJECTION
(caffeine citrate
injection, USP)
60 mg/3 mL
(20 mg/mL)
For Intravenous Use Only
3 mL Single Dose Vial

NDC 0641-6164-10 Rx only
CAFCIT®
INJECTION
(caffeine citrate
injection, USP)
60 mg/3 mL
(20 mg/mL)
For Intravenous Use Only
10 x 3 mL Single Dose Vials